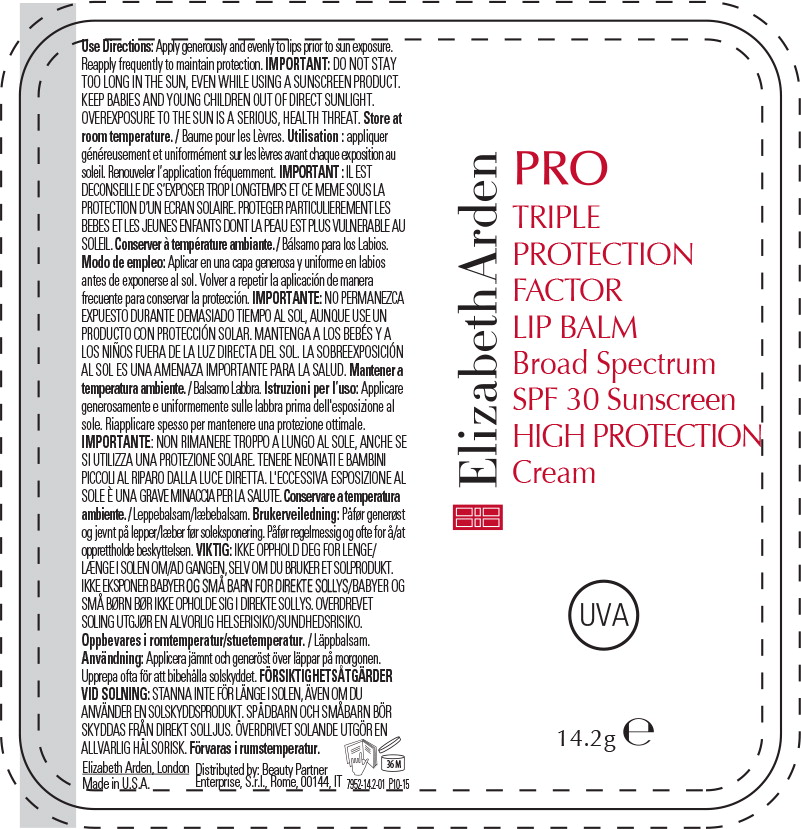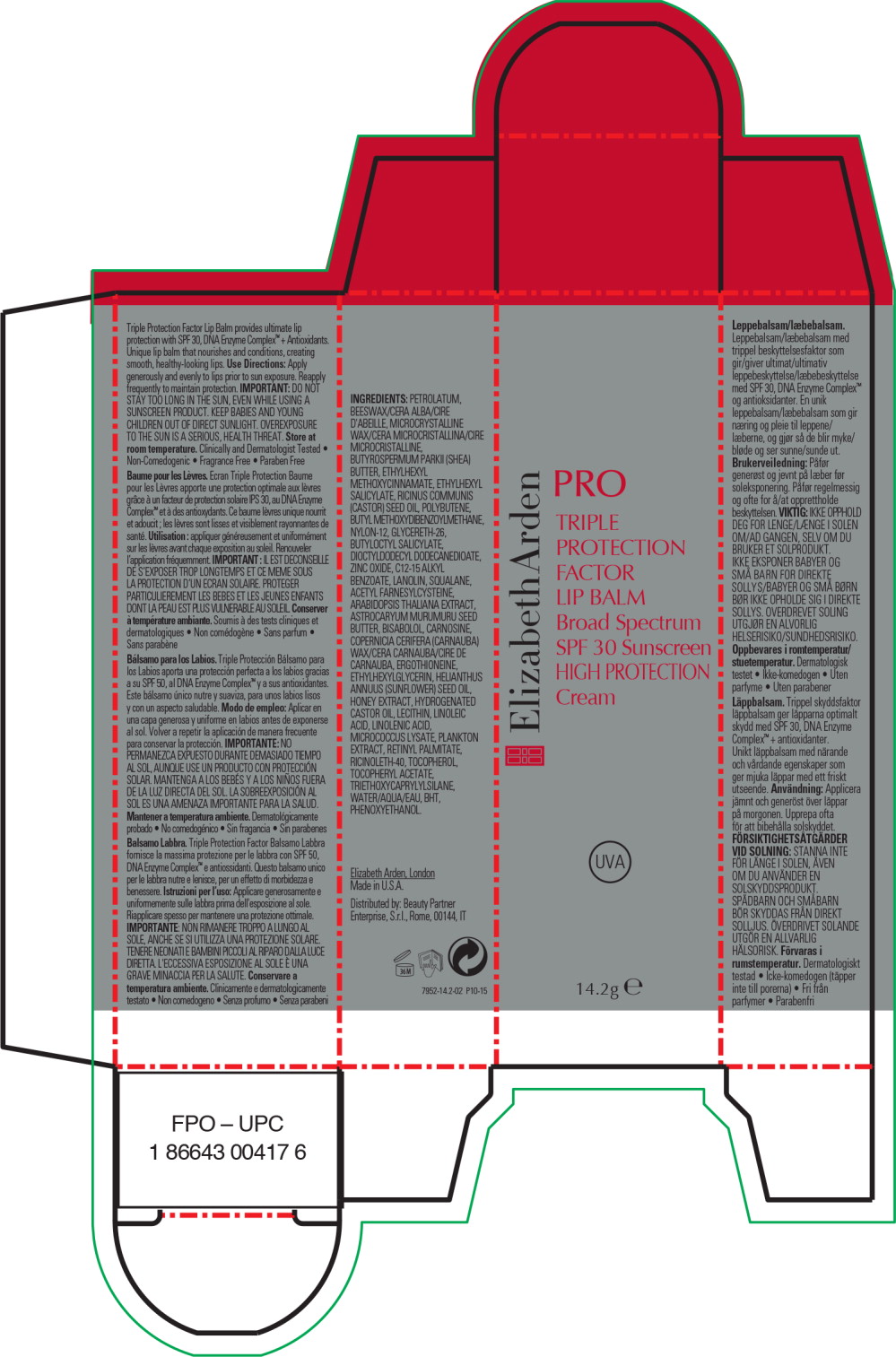 DRUG LABEL: PRO TRIPLE PROTECTION FACTOR LIP BALM BROAD SPECTRUM SPF 30 SUNSCREEN
NDC: 67938-2082 | Form: LOTION
Manufacturer: ELIZABETH ARDEN, INC
Category: otc | Type: HUMAN OTC DRUG LABEL
Date: 20170201

ACTIVE INGREDIENTS: OCTINOXATE 1.065 g/14.2 g; OCTISALATE .71 g/14.2 g; AVOBENZONE .426 g/14.2 g; ZINC OXIDE .142 g/14.2 g
INACTIVE INGREDIENTS: PETROLATUM; YELLOW WAX; MICROCRYSTALLINE WAX; SHEA BUTTER; CASTOR OIL; GLYCERETH-26; NYLON-12; DIOCTYLDODECYL DODECANEDIOATE; BUTYLOCTYL SALICYLATE; SQUALANE; ALKYL (C12-15) BENZOATE; LANOLIN; HYDROGENATED CASTOR OIL; .ALPHA.-TOCOPHEROL ACETATE; WATER; PHENOXYETHANOL; ASTROCARYUM MURUMURU SEED BUTTER; SUNFLOWER OIL; RICINOLETH-40; LEVOMENOL; LINOLEIC ACID; ACETYL FARNESYLCYSTEINE; VITAMIN A PALMITATE; CARNAUBA WAX; LINOLENIC ACID; ETHYLHEXYLGLYCERIN; TRIETHOXYCAPRYLYLSILANE; CARNOSINE; BUTYLATED HYDROXYTOLUENE; TOCOPHEROL; ARABIDOPSIS THALIANA; HONEY; ERGOTHIONEINE

Triple Protection Factor Lip Balm provides ultimate lip protection with SPF 30, DNA Enzyme Complex™ + Antioxidants.

Unique lip balm that nourishes and conditions, creating smooth, healthy-looking lips.

Use Directions:

Apply generously and evenly to lips prior to sun exposure.

Reapply frequently to maintain protection.

IMPORTANT:

DO NOT STAY TOO LONG IN THE SUN, EVEN WHILE USING A SUNSCREEN PRODUCT. KEEP BABIES AND YOUNG CHILDREN OUT OF DIRECT SUNLIGHT. OVEREXPOSURE TO THE SUN IS A SERIOUS, HEALTH THREAT.

Store at room temperature.

Clinically and Dermatologist Tested

- Non-Comedogenic
- Fragrance Free
- Paraben Free

INGREDIENTS:

PETROLATUM, BEESWAX/CERA ALBA/CIRE D'ABEILLE, MICROCRYSTALLINE WAX/CERA MICROCRISTALLINA/CIRE MICROCRISTALLINE, BUTYROSPERMUM PARKII (SHEA) BUTTER, ETHYLHEXYL METHOXYCINNAMATE, ETHYLHEXYL SALICYLATE, RICINUS COMMUNIS (CASTOR) SEED OIL, POLYBUTENE, BUTYL METHOXYDIBENZOYLMETHANE, NYLON-12, GLYCERETH-26, BUTYLOCTYL SALICYLATE, DIOCTYLDODECYL DODECANEDIOATE, ZINC OXIDE, C12-15 ALKYL BENZOATE, LANOLIN, SQUALANE, ACETYL FARNESYLCYSTEINE, ARABIDOPSIS THALIANA EXTRACT, ASTROCARYUM MURUMURU SEED BUTTER, BISABOLOL, CARNOSINE, COPERNICIA CERIFERA (CARNAUBA) WAX/CERA CARNAUBA/CIRE DE CARNAUBA, ERGOTHIONEINE, ETHYLHEXYLGLYCERIN, HELIANTHUS ANNUUS (SUNFLOWER) SEED OIL, HONEY EXTRACT, HYDROGENATED CASTOR OIL, LECITHIN, LINOLEIC ACID, LINOLENIC ACID, MICROCOCCUS LYSATE, PLANKTON EXTRACT, RETINYL PALMITATE, RICINOLETH-40, TOCOPHEROL, TOCOPHERYL ACETATE, TRIETHOXYCAPRYLYLSILANE, WATER/AQUA/EAU, BHT, PHENOXYETHANOL.

Elizabeth Arden, London

Made in U.S.A.

Distributed by: Beauty Partner

Enterprise, S.r.l., Rome, 00144, IT

Principal Display Panel - Bottle Label

ElizabethArden

PRO

TRIPLE
PROTECTION
FACTOR
LIP BALM

Broad Spectrum
SPF 30 Sunscreen

HIGH PROTECTION
Cream

UVA

14.ge

Principal Display Panel - Carton Label

ElizabethArden

PRO

TRIPLE
PROTECTION
FACTOR
LIP BALM

Broad Spectrum
SPF 30 Sunscreen

HIGH PROTECTION
Cream

UVA

14.ge